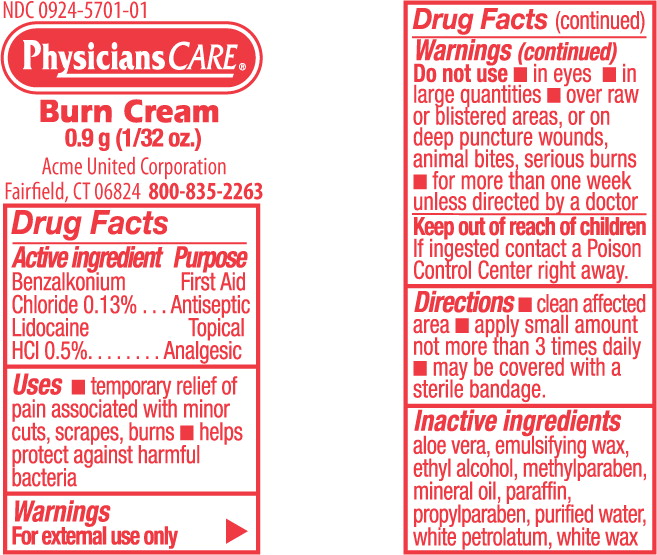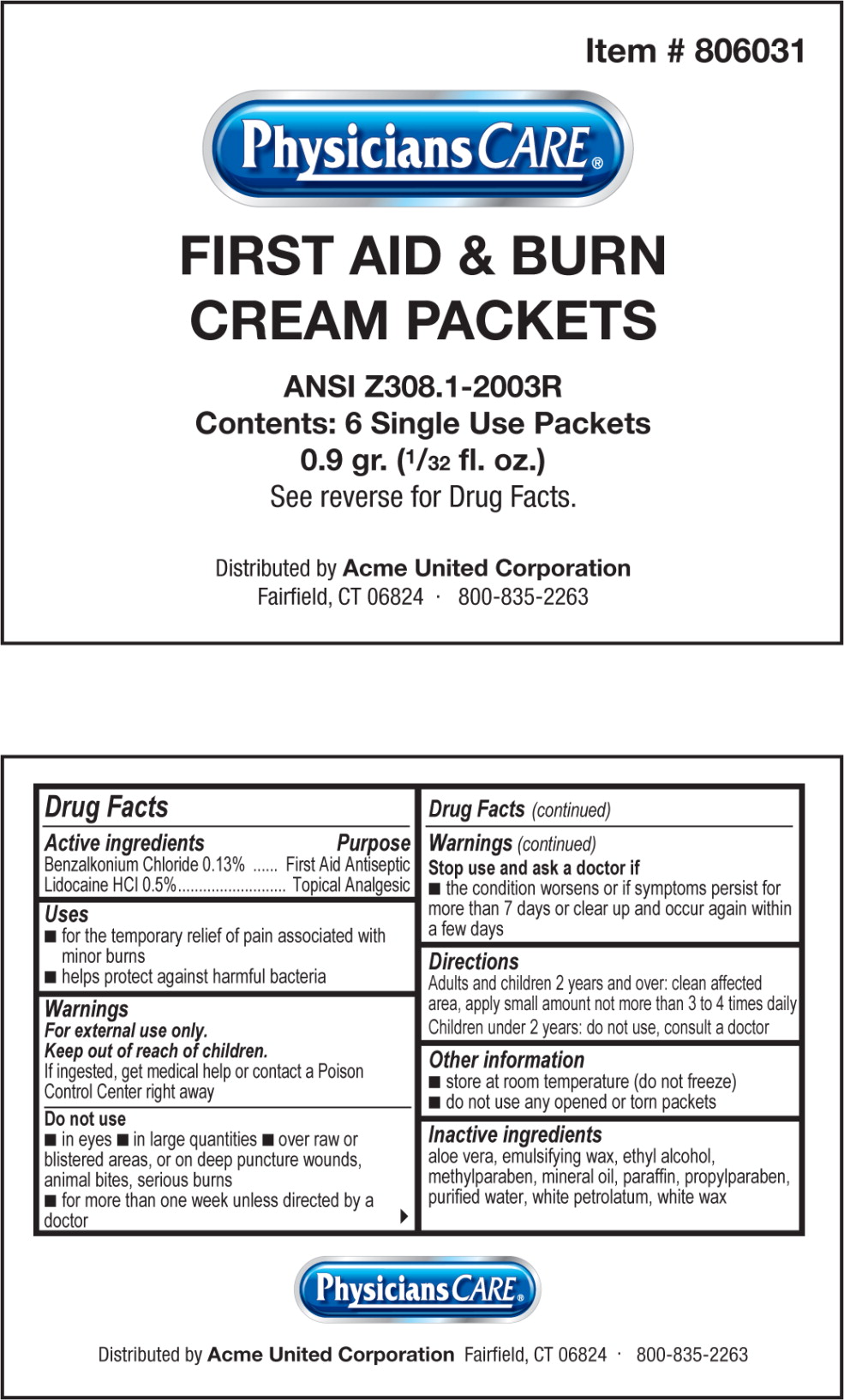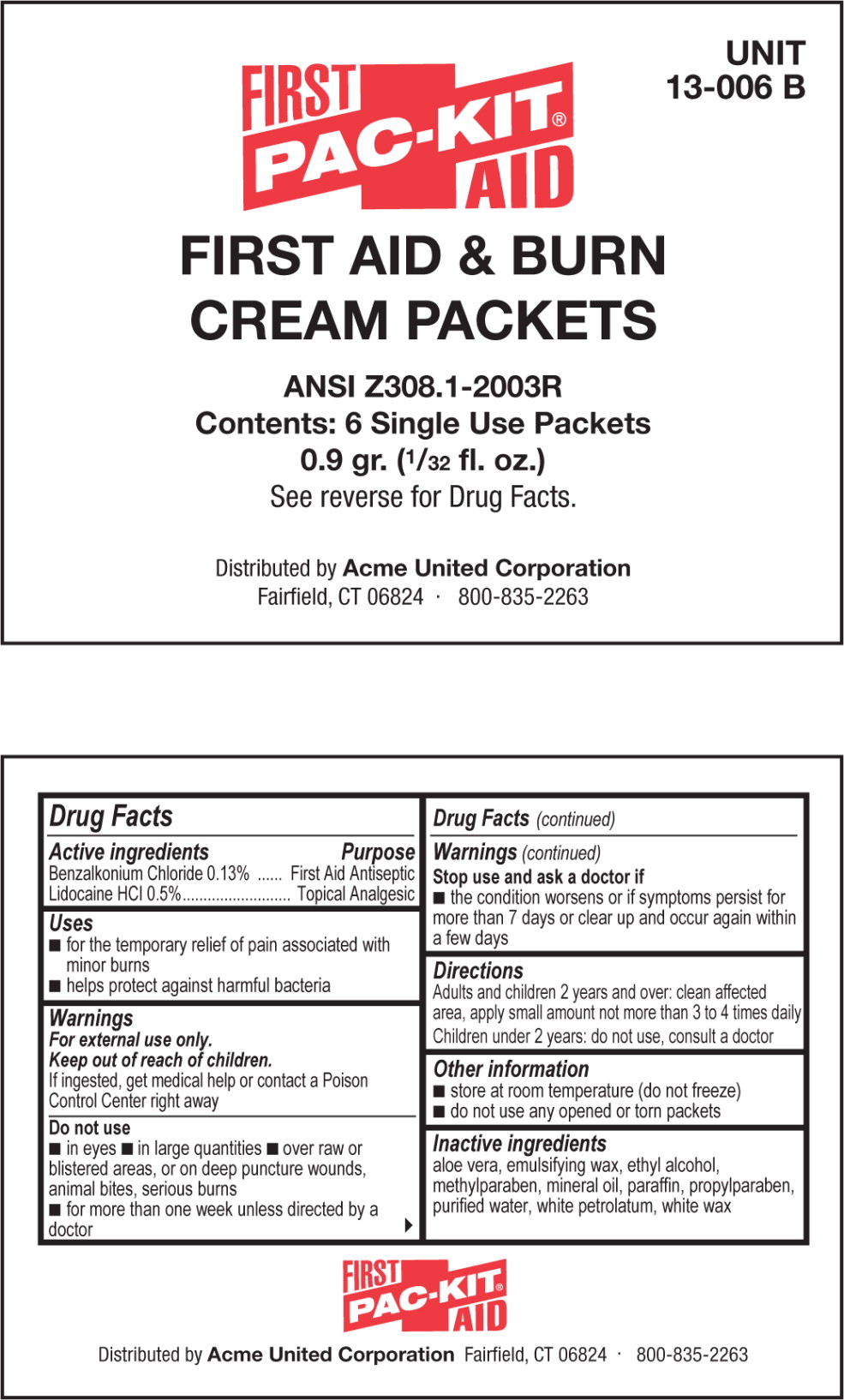 DRUG LABEL: First Aid and Burn
NDC: 0924-5701 | Form: CREAM
Manufacturer: Acme United Corporation
Category: otc | Type: HUMAN OTC DRUG LABEL
Date: 20120127

ACTIVE INGREDIENTS: benzalkonium chloride 1.3 mg/1 g; lidocaine hydrochloride 5 mg/1 g
INACTIVE INGREDIENTS: aloe vera leaf; alcohol; methylparaben; mineral oil; paraffin; propylparaben; water; petrolatum; white wax

Drug Facts

Active Ingredients

Benzalkonium Chloride 0.13%

Lidocaine HCl 0.5%

Purpose

First Aid Antiseptic

Topical analgesic

Uses

- temporary relief of pain associated with minor cuts, scrapes, burns
- helps protect against harmful bacteria

Warnings

For external use only

Do not use

- in eyes
- in large quantities
- over raw or blistered areas, or on deep puncture wounds, animal bites, serious burns
- for more than one week unless directed by a doctor

Keep out of reach of children.

If ingested contact a Poison Control Center right away.

Directions

- clean affected area
- apply small amount not more than 3 times daily
- may be covered with a sterile bandage

Inactive ingredients

aloe vera, emulsifying wax, ethyl alcohol, methylparaben, mineral oil, paraffin, propylparaben, purified water, white petrolatum, white wax

PRINCIPAL DISPLAY PANEL – 0.9 gram packet

NDC 0924-5701-01

PhysiciansCARE

Burn Cream

0.9 g (1/32 oz.)

Acme United Corporation

Fairfield, CT 06824 800-835-2263

PRINCIPAL DISPLAY PANEL – Physicians Care bag (0924-5701-03)

Item # 806031

PhysiciansCARE

FIRST AID & BURN
CREAM PACKETS

ANSI Z308.1-2003R

Contents: 6 Single Use Packets

0.9 gr. (1/32 fl. oz.)

See reverse for Drug Facts.

Distributed by Acme United Corporation

Fairfield, CT 06824 · 800-835-2263

PRINCIPAL DISPLAY PANEL – Pac-Kit bag (0924-5701-02)

Unit 13-006 B

PAC-KIT FIRST AID

FIRST AID & BURN
CREAM PACKETS

ANSI Z308.1-2003R

Contents: 6 Single Use Packets

0.9 gr. (1/32 fl. oz.)

See reverse for Drug Facts.

Distributed by Acme United Corporation

Fairfield, CT 06824 · 800-835-2263